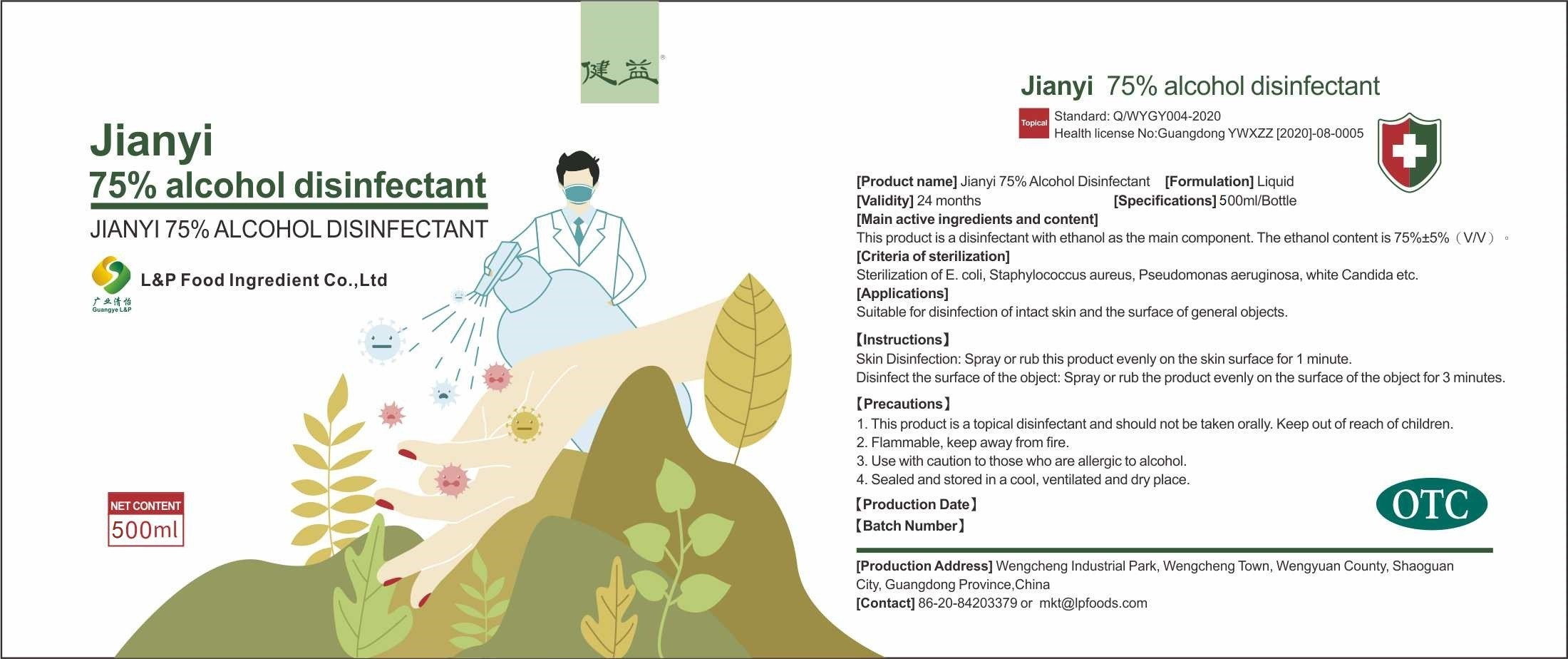 DRUG LABEL: jianyi 75% alcohol disinfectant
NDC: 54380-001 | Form: LIQUID
Manufacturer: L&P Food Ingredient Co., Ltd.
Category: otc | Type: HUMAN OTC DRUG LABEL
Date: 20200423

ACTIVE INGREDIENTS: ALCOHOL 395 mL/500 mL
INACTIVE INGREDIENTS: WATER

DOSAGE AND ADMINISTRATION

Sealed and stored in a cool, ventilated and dry place.

INACTIVE INGREDIENT

purified water

INDICATIONS AND USAGE

Spray or rub this product evenly on the skin surface for 1 minute.
Disinfect the surface of the object: Spray or rub the product evenly on the surface of the object for 3 minutes.

ACTIVE INGREDIENT

ethyl alcohol

keep out of children

PURPOSE

Disinfection
Sterilization

WARNINGS

1. This product is a topical disinfectant and should not be taken orall Keep out of reach of children.
2. Flammable, keep away from fire.
3. Use with caution to those who are allergic to alcohol.
4. Sealed and stored in a cool, ventilated and dry place.